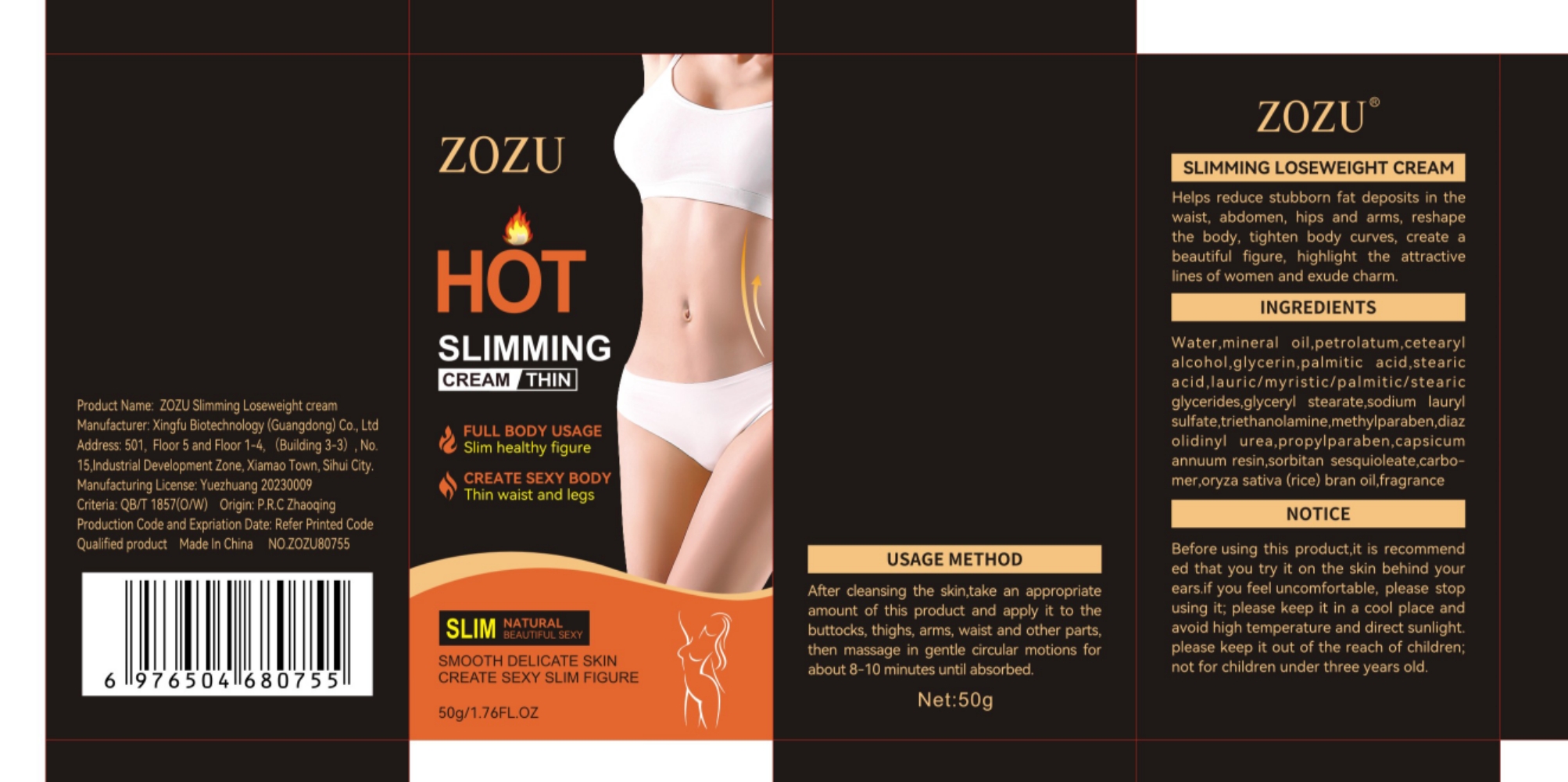 DRUG LABEL: Slimming Cream
NDC: 84372-060 | Form: LOTION
Manufacturer: Shenzhen Zhumeng Times Technology Co., Ltd.
Category: otc | Type: HUMAN OTC DRUG LABEL
Date: 20240914

ACTIVE INGREDIENTS: GLYCERYL MONOSTEARATE 5 g/50 g
INACTIVE INGREDIENTS: MINERAL OIL; TROLAMINE; DIAZOLIDINYL UREA; CAPSICUM OLEORESIN; ORYZANOL; SORBITAN SESQUIOLEATE; METHYLPARABEN; WATER; LAURIC/MYRISTIC DIETHANOLOLAMIDE; CARBOXYPOLYMETHYLENE; STEARIC ACID; GLYCERIN; PALMITIC ACID; PETROLATUM; PROPYLPARABEN; SODIUM LAURYL SULFATE; CETOSTEARYL ALCOHOL

Active ingredients

glyceryl stearate 5%

Purpose

Helps reduce stubborn fat deposits in the
waist,abdomen, hips and arms, reshape
the body,tighten body curves,create a
beautiful figure,highlight the attractive
lines of women and exude charm.

Uses

After ceansing the skintake an appropriate
arount of this product and appy it to the
buttocks,thighs arms,waist and other parts
then massage in gentle circular motions for
about 8-10 minutes until absorbed

Warnings

Before using this productit is recommend
ed that you try it on the skin behind your
earsif you feel uncomfortable, please stop
using it; please keep it in a cool place and
avoid high temperature and direct sunlight
please keep it out of the reach of children
not for children under three years old

Dosage and administration

For external use only.

Do not use

Stop use and ask a doctor if

chest pain, rapid heartbeat, faintness, or dizziness occurs

sudden, unexplained weight gain occurs

your hands or feet swell

scalp irritation or redness occurs

unwanted facial hair growth occurs

you do not see hair regrowth in 4 months

May be harmful if used when pregnant or breast-feeding.

Keep out of reach of children, lf swallowed, get medical help or contact a Poison Control Center right away.

When using section

After ceansing the skintake an appropriate
arount of this product and appy it to the
buttocks,thighs arms,waist and other parts
then massage in gentle circular motions for
about 8-10 minutes until absorbed

stop use

on broken or irritated scalp

Keep out of reach of children

If sxralowed, get medical help or contact a Poison Conirol Cenler ngiht away.

Inactive ingredients

Water,mineral oil,petrolatum,cetearyl

alcohol,glycerin,palmitic acid,stearic

acid,lauric/myristic/palmitic/stearic

glycerides,sodium lauryl

sulfate triethanolamine methylparaben,diaz

olidinyl urea,propylparaben,capsicum

annuum resin,sorbitan sesquioleate,carbo-

mer,oryza sativa(rice) bran oilfragrance